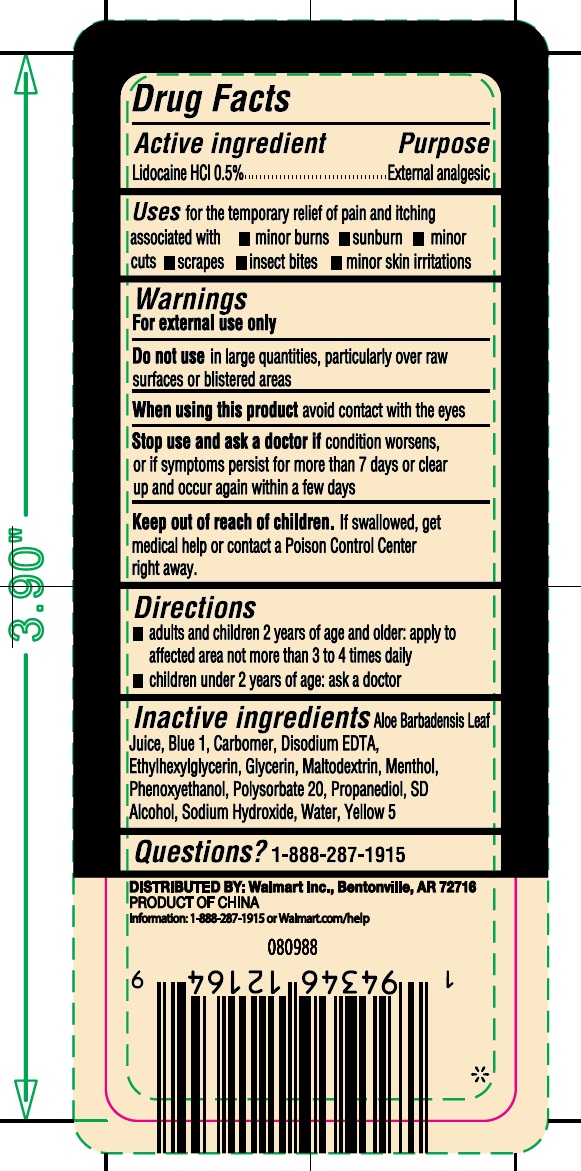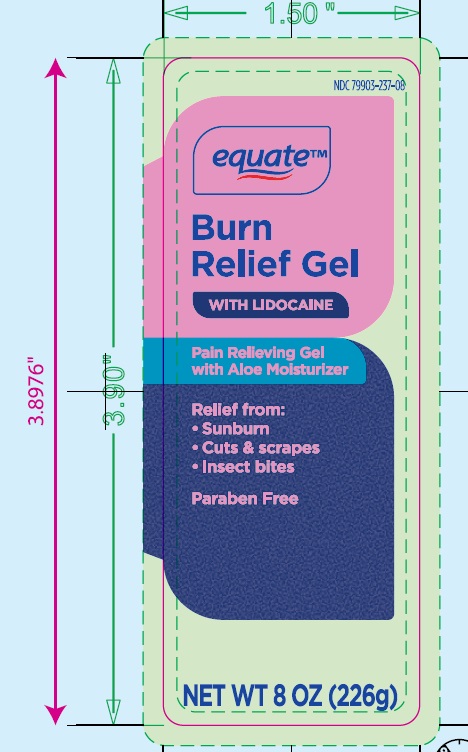 DRUG LABEL: equate Burn Relief
NDC: 79903-237 | Form: GEL
Manufacturer: Walmart Inc
Category: otc | Type: HUMAN OTC DRUG LABEL
Date: 20251002

ACTIVE INGREDIENTS: LIDOCAINE HYDROCHLORIDE 0.5 g/100 g
INACTIVE INGREDIENTS: WATER; ALOE; FD&C BLUE NO. 1; CARBOMER 934; DISODIUM HEDTA; ETHYLHEXYLGLYCERIN; MENTHOL; MALTODEXTRIN; PHENOXYETHANOL; POLYSORBATE 20; PROPANEDIOL; ALCOHOL; SODIUM HYDROXIDE; FD&C YELLOW NO. 5

Walmart 79903-237-08

Active ingredient

Lidocaine HCI 0.5%

Purpose

External analgesic

Uses

for the temporary relief of pain and itching associated with

- minor burns
- sunburn
- minor cuts
- scrapes
- insect bites
- minor skin irritations

Warnings

For external use only.

Do not use in large quantities, particularly over raw surfaces or blistered areas

When using this product avoid contact with eyes

Stop use and ask a doctorif condition worsens, or if symptoms persist for more than 7 days or clearup and occur again within a few days

Keep out of reach of children. If swallowed, get medical help or contact a Poison Control Center right away.

Directions

- adults and children 2 years of age and older: apply to affected area no more than 3 to 4 times daily
- children under 2 years of age: ask a doctor

Inactive ingredients

Aloe Barbadensis Leaf Juice, Blue 1, Carbomer, Disodium EDTA, Ethylhexylglycerin, Glycerin, Maltodextrin, Menthol, Phenoxyethanol, Polysorbate 20, Propanediol, SD Alcohol, Sodium Hydroxide, Water, Yellow 5

PACKAGE LABEL

lebal